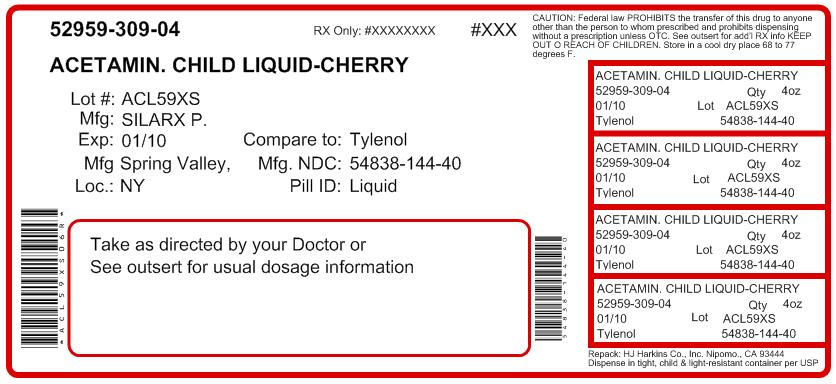 DRUG LABEL: Acetaminophen
NDC: 52959-309 | Form: LIQUID
Manufacturer: H.J. Harkins Company, Inc.
Category: otc | Type: HUMAN OTC DRUG LABEL
Date: 20111208

ACTIVE INGREDIENTS: Acetaminophen 160 mg/5 mL
INACTIVE INGREDIENTS: anhydrous citric acid; D&C red no. 33; FD&C red no. 40; methylparaben; propylene glycol; saccharin sodium; sodium benzoate; water

Children's Silapap Liquid

Active Ingredient: Acetaminophen 160 mg (in each 5 mL = 1 teaspoonful)

Purpose: Pain reliever/fever reducer

INDICATIONS AND USAGE

Uses temporarily relieves minor aches and pains due to: the common cold

- flu
- headache
- sore throat
- toothache
- temporarily reduces fever

Warnings

Liver Warning:This product contains acetaminophen. Severe liver damage may occur if you take:

- more than 5 of the recommended doses per day
- with other drugs containing acetaminophen
- 3 or more alcoholic drinks every day while using this product

Sore throat warning: if sore throat is severe, persists for more than 2 days, is accompanied or followed by fever, headache, rash, nausea or vomiting, consult a doctor promptly.

Alcohol warning:If you consume 3 or more alcoholic drinks every day, ask your doctor whether you should take acetaminophen or other pain relievers/fever reducers.

Do not use

- with any other product containing acetaminophen.

When using this product

- do not exceed recommended dose (see overdose warning)

Stop use and ask a doctor if

- new symptoms occur
- redness or swelling is present
- pain gets worse or lasts for more than 5 days
- fever gets worse or lasts for more than 3 days

Keep out of reach of children.

OVERDOSAGE

Overdose Warning: Taking more than the recommended dose (overdose) may cause liver damage. In case of overdose, get medical help or contact a Poison Control Center right away. Quick medical attention is critical even if you do not notice any signs of symptoms.

Directions

- do not take more than directed (see overdose warning).
- if needed, repeat dose every 4 hours or as directed by a doctor
- do not give more than 5 doses in 24 hours

children under 2 yrs (under 24 lbs) | ask a doctor
children 2-3 years (24-35 lbs) | 1 teaspoonful (5 mL)
children 4-5 years (36-47 lbs) | 1 1/2 teaspoonfuls (7.5 mL)
children 6-8 years (48-59 lbs) | 2 teaspoonfuls (10 mL)
children 9-10 years (60-71 lbs) | 2 1/2 teaspoonfuls (12.5 mL)
children 11 years (72-95 lbs) | 3 teaspoonfuls (15 mL)
adults & children 12 years & older | 4 teaspoonfuls (20 mL)

Other information
Store at room temperature 20°-25°C (68°-77°F)

Inactive ingredients

citric acid, D&C red no. 33, FD&C red no. 40, cherry flavor, methylparaben, propylene glycol, saccharin sodium, sodium benzoate, and purified water.

Questions

888-974-5279

This product is not manufactured or distributed by McNeil Consumer & Specialty Pharmaceuticals, distributor of Tylenol®.

Manufactured by:

Silarx Pharmaceuticals, Inc
19 West Street
Spring Valley, NY 10977
USA

Repacked by:

H.J. Harkins Company, Inc.
513 Sandydale Drive
Nipomo, CA 93444
USA